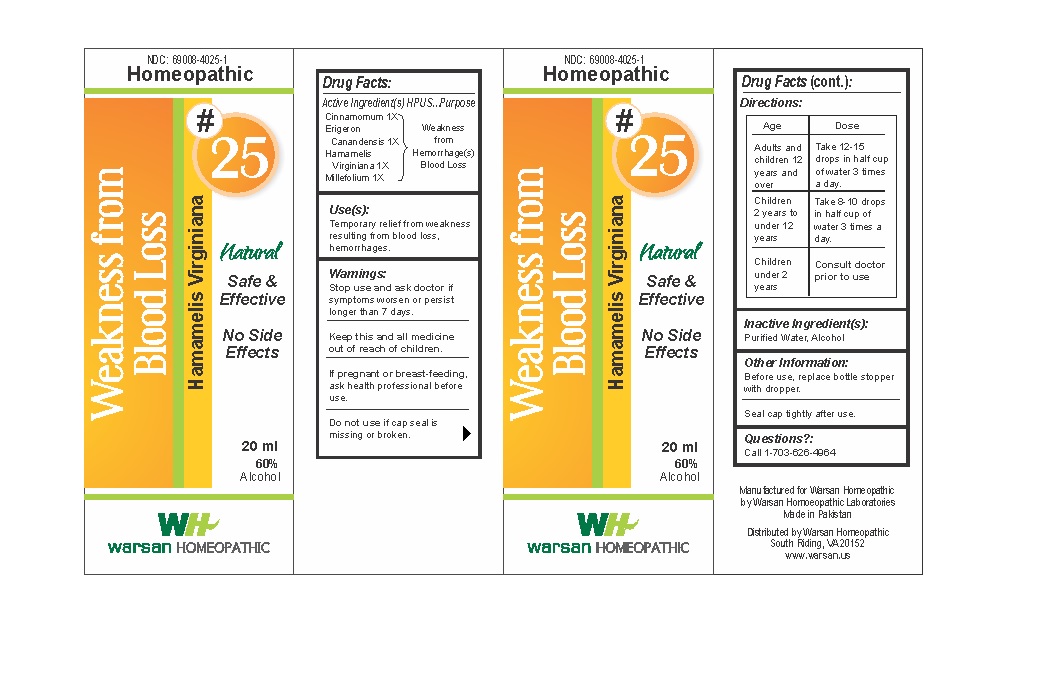 DRUG LABEL: Combination Remedy 25 - Weakness from Blood Loss
NDC: 69008-4025 | Form: SOLUTION/ DROPS
Manufacturer: Warsan Homoeopathic Laboratories
Category: homeopathic | Type: HUMAN OTC DRUG LABEL
Date: 20171225

ACTIVE INGREDIENTS: HAMAMELIS VIRGINIANA ROOT BARK/STEM BARK 1 [hp_X]/1 mL; ACHILLEA MILLEFOLIUM 1 [hp_X]/1 mL; CINNAMON 1 [hp_X]/1 mL; CONYZA CANADENSIS 1 [hp_X]/1 mL
INACTIVE INGREDIENTS: ALCOHOL; WATER

Stop use and ask doctor if symptoms worsen or persist longer than 7 days.

If pregnant or breast-feeding, ask health professional before use.

Do not use if tamper evident seal is missing or broken.

Keep out of reach of children.

ACTIVE INGREDIENT

Cinnamomum 1X

Erigeron Canandensis 1X

Hamamelis Virginiana 1X

Millefolium 1X

PURPOSE

Temporary relief from weakness resulting from blood loss, hemorrhages..

INACTIVE INGREDIENT

Purified Water

Alcohol

DOSAGE AND ADMINISTRATION

Adults and children 12 years and older: Take 10-15 drops in half cup of water 3 times a day.

Children 2 years to under 12 years: Take 8-10 drops in half cup of water of 3 times a day.

Children under 2 years: Consult doctor prior to use.

INDICATIONS AND USAGE

Temporary relief from weakness resulting from blood loss, hemorrhages.